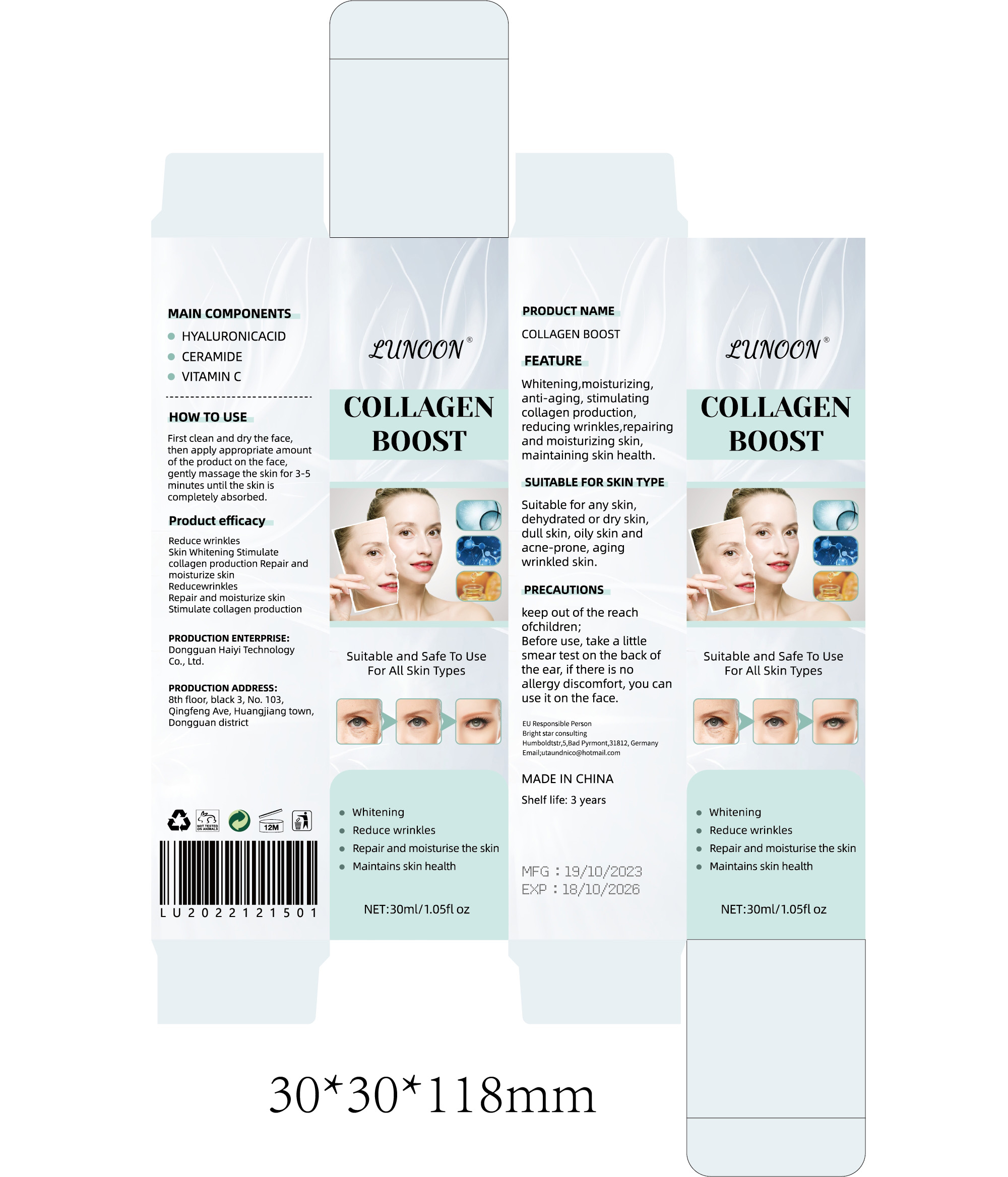 DRUG LABEL: COLLAGEN BOOST
NDC: 84732-013 | Form: CREAM
Manufacturer: Dongguan Haiyi Technology Co.,Ltd.
Category: otc | Type: HUMAN OTC DRUG LABEL
Date: 20240925

ACTIVE INGREDIENTS: HYALURONIC ACID 1 mg/30 mL
INACTIVE INGREDIENTS: CERAMIDE 1; ASCORBIC ACID

Active ingredient

HYALURONIC ACID

Inactive ingredient

● CERAMIDE
● VITAMIN C

Purpose section

Reduce wrinkles

Skin Whitening Stimulate collagen production Repair and moisturize skin

Reducewrinkles

Repair and moisturize skin

Stimulate collagen production

Warning

keep out of the reach of children;
Before use, take a little smear test on the back oft he ear,if there is no allergy discomfort,you can use it on the face.

stop use

This product may cause allergic reactions in asmall number of people.
lf youexperience any discomfort,please stop using it immediately.

OUT OF CHILDREN

KEEP THE PRODUCT OUT OF REACH OF CHILDREN to

HOW TO USE

First clean and dry the face,then apply appropriate amount of the product on the face,gently massage the skin for 3-5minutes until the skin is completely absorbed.

Dosage

take an appropriateamount,Use 2-3 times a week

not use

Not suitable for use by children, pregnantor breastfeeding people.